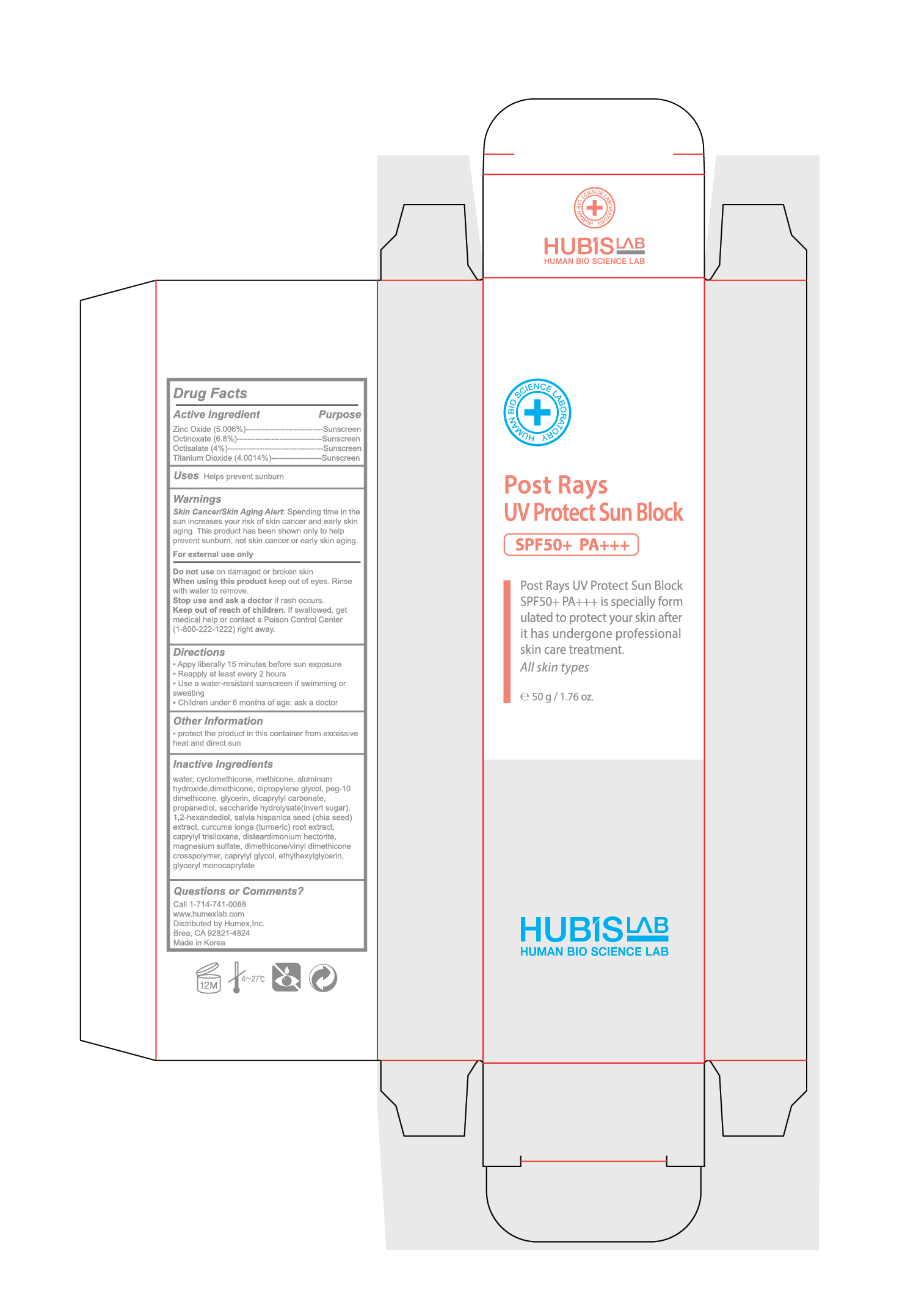 DRUG LABEL: Post Rays UV Protect Sun Block
NDC: 76344-8002 | Form: CREAM
Manufacturer: Humex,Inc
Category: otc | Type: HUMAN OTC DRUG LABEL
Date: 20210111

ACTIVE INGREDIENTS: OCTINOXATE 6.8 g/100 g; OCTISALATE 4.5 g/100 g; TITANIUM DIOXIDE 4.0014 g/100 g; ZINC OXIDE 5.006 g/100 g
INACTIVE INGREDIENTS: CAPRYLYL TRISILOXANE 1 g/100 g; MAGNESIUM SULFATE, UNSPECIFIED 0.8 g/100 g; DISTEARDIMONIUM HECTORITE 0.8 g/100 g; TURMERIC 0.01 g/100 g; GLYCERYL CAPRYLATE 0.1 g/100 g; PEG-10 DIMETHICONE (600 CST) 3 g/100 g; ETHYLHEXYLGLYCERIN 0.1 g/100 g; CYCLOMETHICONE 5 13 g/100 g; DIPROPYLENE GLYCOL 3 g/100 g; INVERT SUGAR 0.1 g/100 g; SALVIA HISPANICA SEED 0.01 g/100 g; CAPRYLYL GLYCOL 0.2 g/100 g; ALUMINUM HYDROXIDE 0.5643 g/100 g; PROPANEDIOL 0.1 g/100 g; 1,2-HEXANEDIOL 0.02 g/100 g; DICAPRYLYL CARBONATE 2 g/100 g; METHICONE (20 CST) 0.2084 g/100 g; DIMETHICONE 0.2565 g/100 g; GLYCERIN 2 g/100 g

Drug Facts Active Ingredient Purpose

Zinc Oxide (5.006%)-----------------------------Sunscreen
Octinoxate (6.8%)--------------------------------Sunscreen
Octisalate (4%)------------------------------------Sunscreen
Titanium Dioxide (4.0014%)-------------------Sunscreen

Uses

Helps prevent sunburn

Warnings

Skin Cancer/Skin Aging Alert: Spending time in the sun increases your risk of skin cancer and early skin aging. This product has been shown only to help prevent sunburn, not skin cancer or early skin aging.

For external use only

Do not use on damaged or broken skin
When using this product keep out of eyes. Rinse with water to remove.
Stop use and ask a doctor if rash occurs.
Keep out of reach of children. If swallowed, get medical help or contact a Poison Control Center (1-800-222-1222) right away.

Directions

▪ Apply liberally 15 minutes before sun exposure
▪ Reapply at least every 2 hours
▪ Use a water-resistant sunscreen if swimming or sweating
▪ Children under 6 months of age: ask a doctor

Other Information

▪ protect the product in this container from excessive heat and direct sun

Inactive Ingredients

water, cyclomethicone, methicone, aluminum hydroxide,dimethicone, dipropylene glycol, peg-10 dimethicone, glycerin, dicaprylyl carbonate, propanediol, saccharide hydrolysate(invert sugar), 1,2-hexandediol, salvia hispanica seed (chia seed) extract, curcuma longa (turmeric) root extract, caprylyl trisiloxane, disteardimonium hectorite, magnesium sulfate, dimethicone/vinyl dimethicone crosspolymer, caprylyl glycol, ethylhexylglycerin, glyceryl monocaprylate